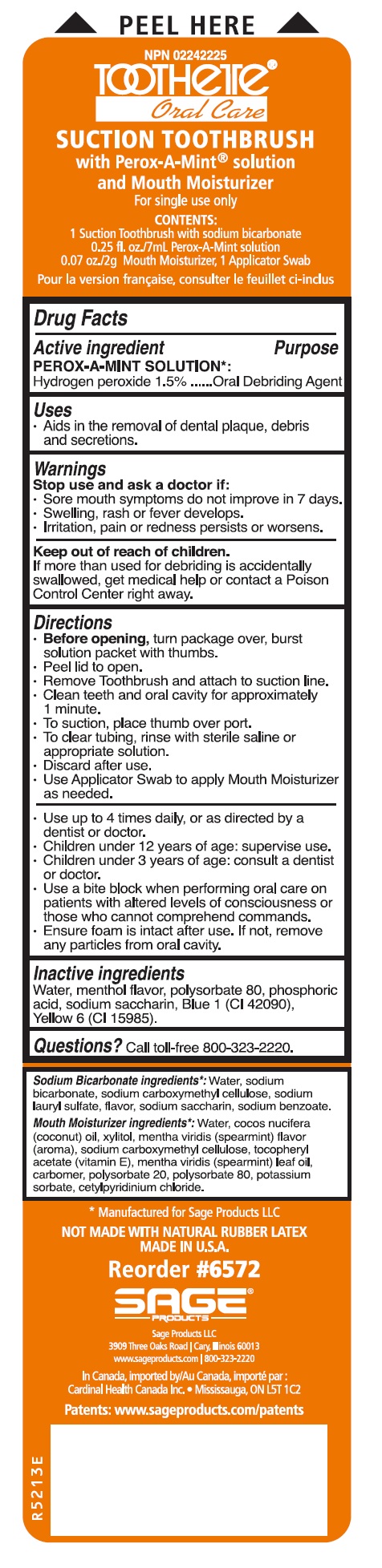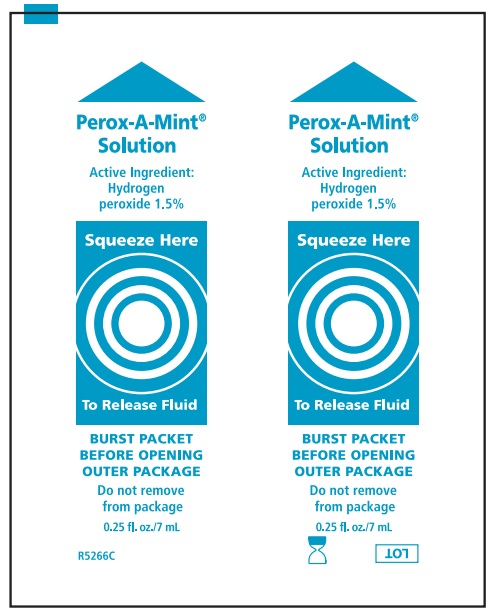 DRUG LABEL: Suction Toothbrush with Perox-A-Mint Solution
NDC: 53462-572 | Form: KIT | Route: BUCCAL
Manufacturer: Sage Products, LLC
Category: otc | Type: HUMAN OTC DRUG LABEL
Date: 20190920

ACTIVE INGREDIENTS: HYDROGEN PEROXIDE 15 mg/1 mL
INACTIVE INGREDIENTS: WATER; POLYSORBATE 80; PHOSPHORIC ACID; SACCHARIN SODIUM; FD&C BLUE NO. 1; FD&C YELLOW NO. 6

Suction Toothbrush with Perox-A-Mint Solution

Drug Facts

Active Ingredients | Purpose
Perox-A-Mint Solution
Hydrogen peroxide 1.5% | Oral Debriding Agent

Uses

- Aids in the removal of dental plaque, debris and secretions.

Warnings

Stop use and ask a doctor if:

- Sore mouth symptoms do not improve in 7 days.
- Swelling, rash or fever develops.
- Irritation, pain or redness persists or worsens.

Keep out of reach of children.

If more than used for debriding is accidentally swallowed, get medical help or contact a Poison Control Center right away.

Directions

Suction Toothbrush with Perox-A-Mint Solution and Mouth Moisturizer

- Before opening, turn package over, burst solution packet with thumbs.
- Peel lid to open.
- Remove toothbrush and attach to suction line.
- Clean teeth and oral cavity for approximately 1 minute.
- To suction, place thumb over port.
- To clear tubing, rinse with sterile saline or appropriate solution.
- Discard after use.
- Use Applicator Swab to apply Mouth Moisturizer as needed.
- Use up to 4 times daily, or as directed by a dentist or doctor.
- Children under 12 years of age: supervise use.
- Children under 3 years of age: consult a dentist or doctor.
- Use a bite block when performing oral care on patients with altered levels of consciousness or those who cannot comprehend commands.
- Ensure foam is intact after use. If not, remove any particles from oral cavity.

Inactive Ingredients

Water, menthol flavor, polysorbate 80, phosphoric acid, sodium saccharin, Blue 1 (CI 42090), Yellow 6 (CI 15985)

Questions

Call toll-free 800-323-2220